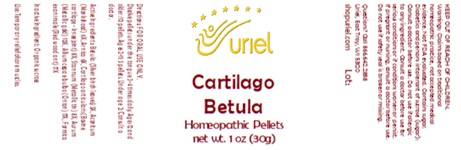 DRUG LABEL: Cartilago Betula
NDC: 48951-3041 | Form: PELLET
Manufacturer: Uriel Pharmacy Inc.
Category: homeopathic | Type: HUMAN OTC DRUG LABEL
Date: 20251208

ACTIVE INGREDIENTS: BETULA PUBESCENS LEAF 5 [hp_X]/1 1; ACONITUM NAPELLUS 6 [hp_X]/1 1; ARNICA MONTANA 6 [hp_X]/1 1; BOS TAURUS CARTILAGE 8 [hp_X]/1 1; TIN 8 [hp_X]/1 1; GOLD 10 [hp_X]/1 1; ONION 17 [hp_X]/1 1; FORMICA RUFA 17 [hp_X]/1 1
INACTIVE INGREDIENTS: SUCROSE

Cartilago Betula

INDICATIONS AND USAGE

Directions: FOR ORAL USE ONLY.

DOSAGE AND ADMINISTRATION

Dissolve pellets under the tongue 3-4
times daily. Ages 12 and older: 10 pellets.
Ages 2-11: 5 pellets. Under age 2: Consult
a doctor.

ACTIVE INGREDIENT

Active Ingredients: Betula (Silver birch leaves) 5X, Aconitum (Monkshood) 6X, Arnica 6X, Cartilago articularis (Bovine cartilage - knee joint) 8X, Stannum (Metallic tin) 8X, Aurum (Metallic gold) 10X, Allium cepa e bulbo (Onion) 17X, Formica ex animale (Red wood ant) 17X

Inactive Ingredient: Organic sucrose

Prepared using rhythmical processes.

PURPOSE

Use: Temporary relief of sore muscles.

KEEP OUT OF REACH OF CHILDREN.

WARNINGS

Warnings: Claims based on traditional homeopathic practice, not accepted medical evidence. Not FDA evaluated. Contains sugar. Diabetics and persons intolerant of sucrose (sugar): Consult a doctor before use. Do not use if allergic to any ingredient. Consult a doctor before use for serious conditions or if conditions worsen or persist. If pregnant or nursing, consult a doctor before use. Do not use if safety seal is broken or missing.

Questions? Call 866.642.2858
Uriel, East Troy, WI 53120
shopuriel.com Lot: